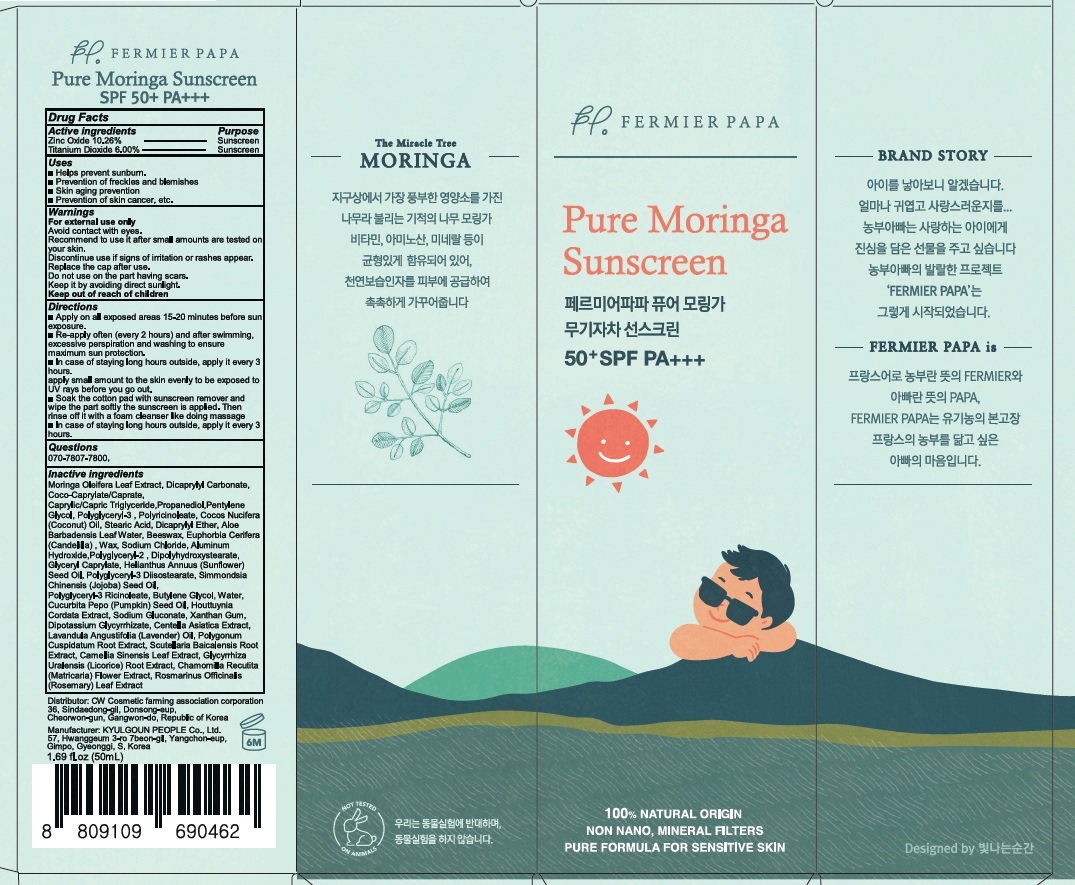 DRUG LABEL: FERMIERPAPA Pure Moringa Sunscreen
NDC: 81482-010 | Form: CREAM
Manufacturer: Cheolwon Cosmetic Farming Association
Category: otc | Type: HUMAN OTC DRUG LABEL
Date: 20210201

ACTIVE INGREDIENTS: Zinc Oxide 5.13 g/50 g; Titanium Dioxide 3.00 g/50 g
INACTIVE INGREDIENTS: MORINGA OLEIFERA LEAF; Dicaprylyl Carbonate

ACTIVE INGREDIENTS

Zinc Oxide 10.26%
Titanium Dioxide 6.00%

INACTIVE INGREDIENTS

Moringa Oleifera Leaf Extract, Dicaprylyl Carbonate, Coco-Caprylate/Caprate, Caprylic/Capric Triglyceride,Propanediol,Pentylene Glycol, Polyglyceryl-3 , Polyricinoleate, Cocos Nucifera (Coconut) Oil, Stearic Acid, Dicaprylyl Ether, Aloe Barbadensis Leaf Water, Beeswax, Euphorbia Cerifera (Candelilla) , Wax, Sodium Chloride, Aluminum Hydroxide,Polyglyceryl-2 , Dipolyhydroxystearate, Glyceryl Caprylate, Helianthus Annuus (Sunflower) Seed Oil, Polyglyceryl-3 Diisostearate, Simmondsia Chinensis (Jojoba) Seed Oil, Polyglyceryl-3 Ricinoleate, Butylene Glycol, Water, Cucurbita Pepo (Pumpkin) Seed Oil, Houttuynia Cordata Extract, Sodium Gluconate, Xanthan Gum, Dipotassium Glycyrrhizate, Centella Asiatica Extract, Lavandula Angustifolia (Lavender) Oil, Polygonum Cuspidatum Root Extract, Scutellaria Baicalensis Root Extract, Camellia Sinensis Leaf Extract, Glycyrrhiza Uralensis (Licorice) Root Extract, Chamomilla Recutita (Matricaria) Flower Extract, Rosmarinus Officinalis (Rosemary) Leaf Extract

PURPOSE

Sunscreen

WARNINGS

For external use only
Avoid contact with eyes.
Recommend to use it after small amounts are tested on your skin.
Discontinue use if signs of irritation or rashes appear.
Replace the cap after use.
Do not use on the part having scars.
Keep it by avoiding direct sunlight.
Keep out of reach of children

DESCRIPTION

Uses
■ Helps prevent sunburn.
■ Prevention of freckles and blemishes
■ Skin aging prevention
■ Prevention of skin cancer, etc.

Directions
■ Apply on all exposed areas 15-20 minutes before sun exposure.
■ Re-apply often (every 2 hours) and after swimming, excessive perspiration and washing to ensure maximum sun protection.
■ In case of staying long hours outside, apply it every 3 hours.
apply small amount to the skin evenly to be exposed to UV rays before you go out.
■ Soak the cotton pad with sunscreen remover and wipe the part softly the sunscreen is applied. Then rinse off it with a foam cleanser like doing massage
■ In case of staying long hours outside, apply it every 3 hours.

Questions
070-7807-7800
https://fermierpapa.com